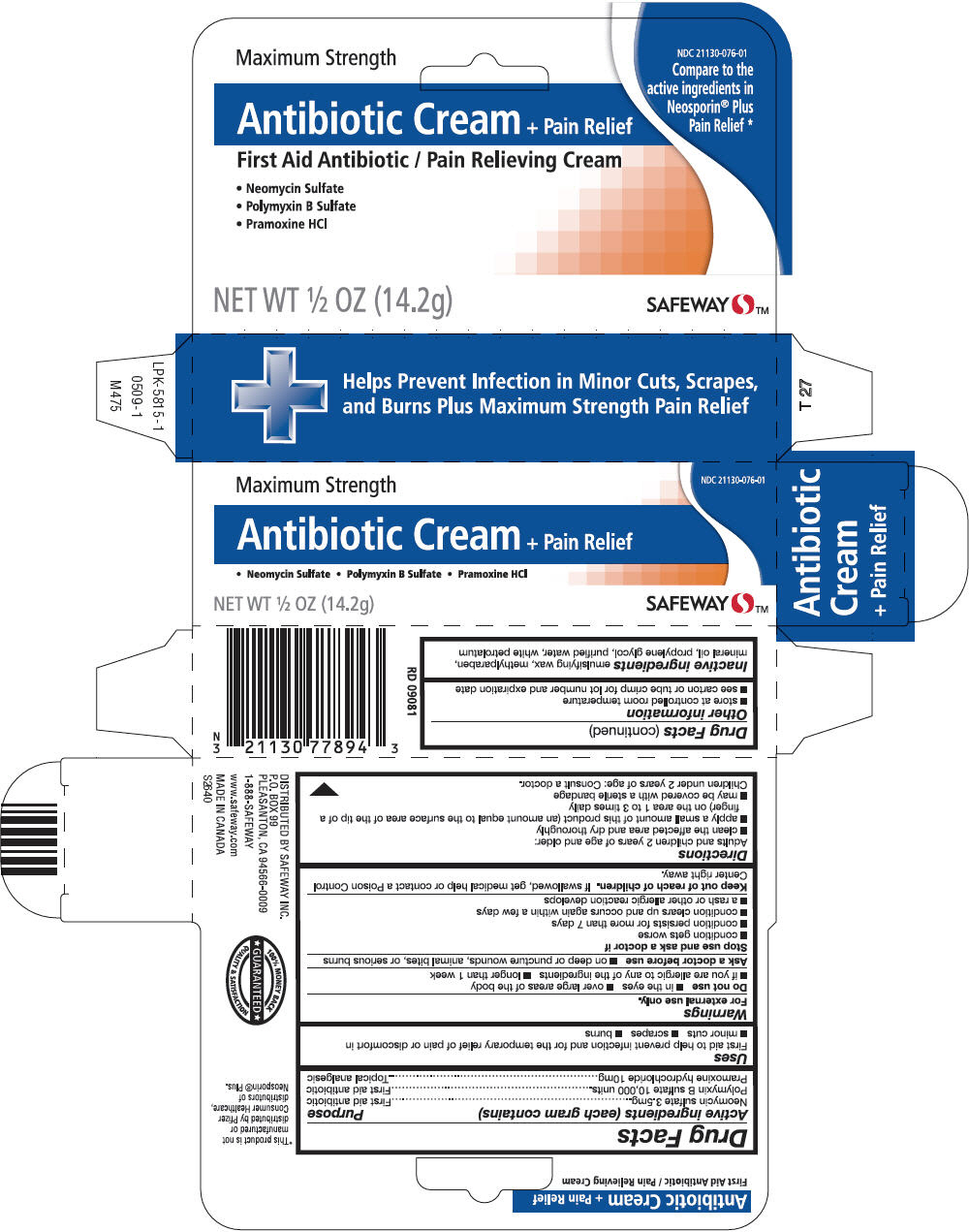 DRUG LABEL: Safeway 
NDC: 21130-076 | Form: CREAM
Manufacturer: Safeway Inc
Category: otc | Type: HUMAN OTC DRUG LABEL
Date: 20130306

ACTIVE INGREDIENTS: Neomycin Sulfate 3.5 mg/1 g; Polymyxin B Sulfate 10000 [iU]/1 g; Pramoxine Hydrochloride 10 mg/1 g
INACTIVE INGREDIENTS: METHYLPARABEN; MINERAL OIL; PROPYLENE GLYCOL; WATER; PETROLATUM

Safeway™
Antibiotic Plus Pain Relief

Drug Facts

ACTIVE INGREDIENT

Active ingredients (each gram contains) | Purpose
Neomycin sulfate 3.5mg | First aid antibiotic
Polymyxin B sulfate 10,000 units | First aid antibiotic
Pramoxine hydrochloride 10mg | Topical analgesic

Uses

First aid to help prevent infection and for the temporary relief of pain or discomfort in

- minor cuts
- scrapes
- burns

Warnings

For external use only.

Do not use

- in the eyes
- over large areas of the body
- if you are allergic to any of the ingredients
- longer than 1 week

Ask a doctor before use

- on deep or puncture wounds, animal bites, or serious burns

Stop use and ask a doctor if

- condition gets worse
- condition persists for more than 7 days
- condition clears up and occurs again within a few days
- a rash or other allergic reaction develops

Keep out of reach of children. If swallowed, get medical help or contact a Poison Control Center right away.

Directions

Adults and children 2 years of age and older:

- clean the affected area and dry thoroughly
- apply a small amount of this product (an amount equal to the surface area of the tip of a finger) on the area 1 to 3 times daily
- may be covered with a sterile bandage

Children under 2 years of age: Consult a doctor.

Other information

- store at controlled room temperature
- see carton or tube crimp for lot number and expiration date

Inactive ingredients

emulsifying wax, methylparaben, mineral oil, propylene glycol, purified water, white petrolatum

DISTRIBUTED BY SAFEWAY INC.
P.O. BOX 99
PLEASANTON, CA 94566-0009

1-888-SAFEWAY

PRINCIPAL DISPLAY PANEL - 14.2g Tube Carton

Maximum Strength

NDC 21130-076-01

Antibiotic Cream + Pain Relief

• Neomycin Sulfate • Polymyxin B Sulfate • Pramoxine HCl

NET WT ½ OZ (14.2g)

SAFEWAY™